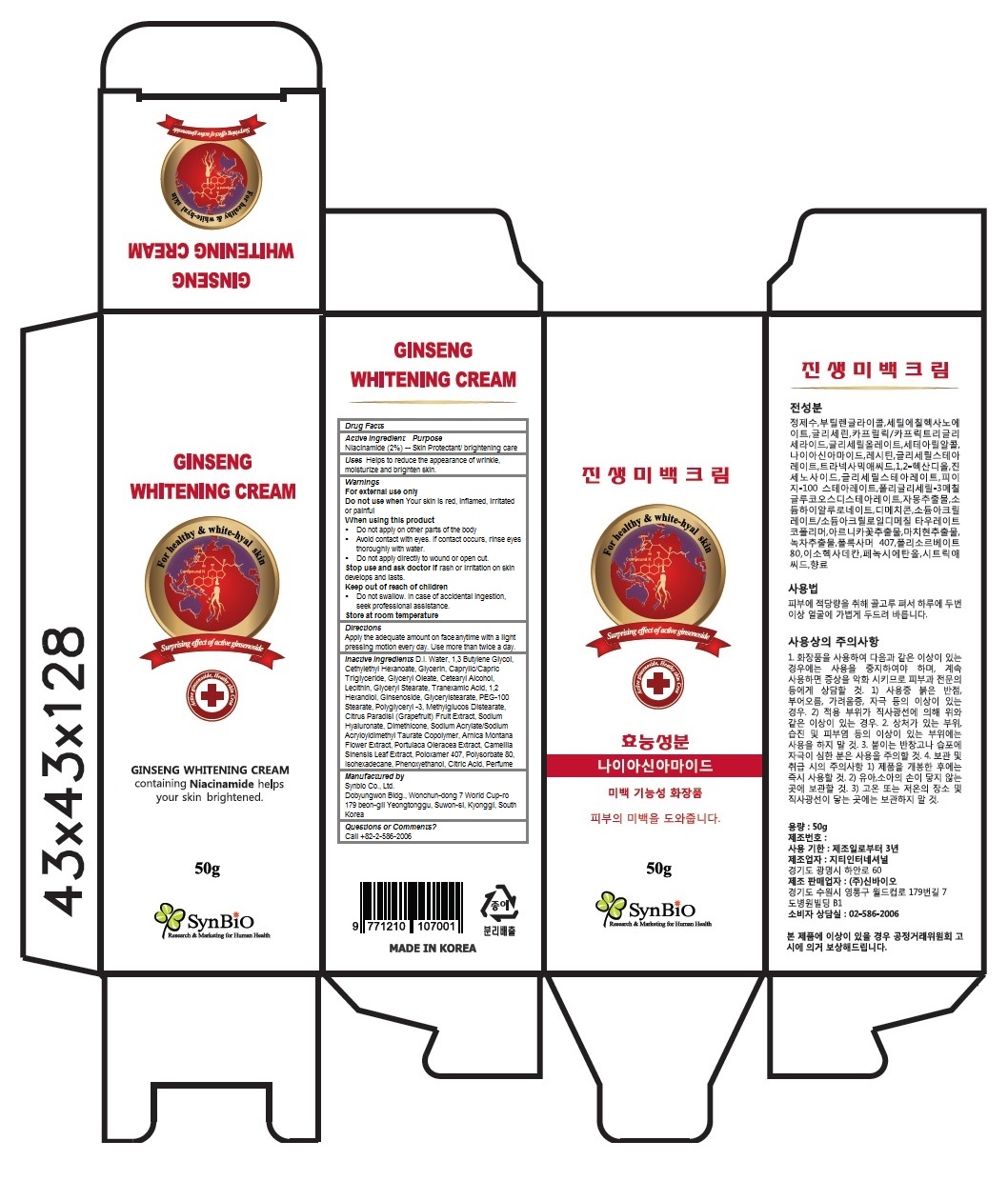 DRUG LABEL: Ginseng Whitening
NDC: 70969-101 | Form: CREAM
Manufacturer: Synbio Co., Ltd.
Category: otc | Type: HUMAN OTC DRUG LABEL
Date: 20160919

ACTIVE INGREDIENTS: Niacinamide 2 g/50 g
INACTIVE INGREDIENTS: WATER; CETYL ETHYLHEXANOATE; Glycerin; MEDIUM-CHAIN TRIGLYCERIDES; Glyceryl Oleate; CETOSTEARYL ALCOHOL; EGG PHOSPHOLIPIDS; GLYCERYL MONOSTEARATE; TRANEXAMIC ACID; 1,2-HEXANEDIOL; GINSENOSIDES; PEG-100 STEARATE; POLYGLYCERIN-3; GRAPEFRUIT; HYALURONATE SODIUM; Dimethicone; SODIUM ACRYLATE/SODIUM ACRYLOYLDIMETHYLTAURATE COPOLYMER (4000000 MW); ARNICA MONTANA FLOWER; PURSLANE; GREEN TEA LEAF; POLOXAMER 407; POLYSORBATE 80; ISOHEXADECANE; PHENOXYETHANOL; CITRIC ACID MONOHYDRATE

Ginseng Whitening Cream

Active Ingredients

Niacinamide (2%)

Purpose

Skin Protectant/ brightening care

Uses

Helps to reduce the appearance of wrinkle, moisturize and brighten skin.

Keep out of reach of children

Do not swallow. In case of accidental ingestion, seek professional assistance.

Warnings

For external use only
Do not use when Your skin is red, inflamed, irritated or painful
When using this product
- Do not apply on other parts of the body
- Avoid contact with eyes. If contact occurs, rinse eyes thoroughly with water.
- Do not apply directly to wound or open cut.
Stop use and ask doctor if rash or irritation on skin develops and lasts.
Store at room temperature

Directions

Apply the adequate amount on skin anytime with a light pressing motion every day. Use more than twice a day.

Inactive Ingredients

D.I. Water, 1,3 Butylene Glycol, Cethylethyl Hexanoate, Glycerin, Caprylic/Capric Triglyceride, Glyceryl Oleate, Cetearyl Alcohol, Lecithin, Glyceryl Stearate, Tranexamic Acid, 1,2 Hexandiol, Ginsenoside, Glycerylstearate, PEG-100 Stearate, Polyglyceryl -3, Methylglucos Distearate, Citrus Paradisi (Grapefruit) Fruit Extract, Sodium Hyaluronate, Dimethicone, Sodium Acrylate/Sodium Acryloyldimethyl Taurate Copolymer, Arnica Montana Flower Extract, Portulaca Oleracea Extract, Camellia Sinensis Leaf Extract, Poloxamer 407, Polysorbate 80, Isohexadecane, Phenoxyethanol, Citric Acid, Perfume